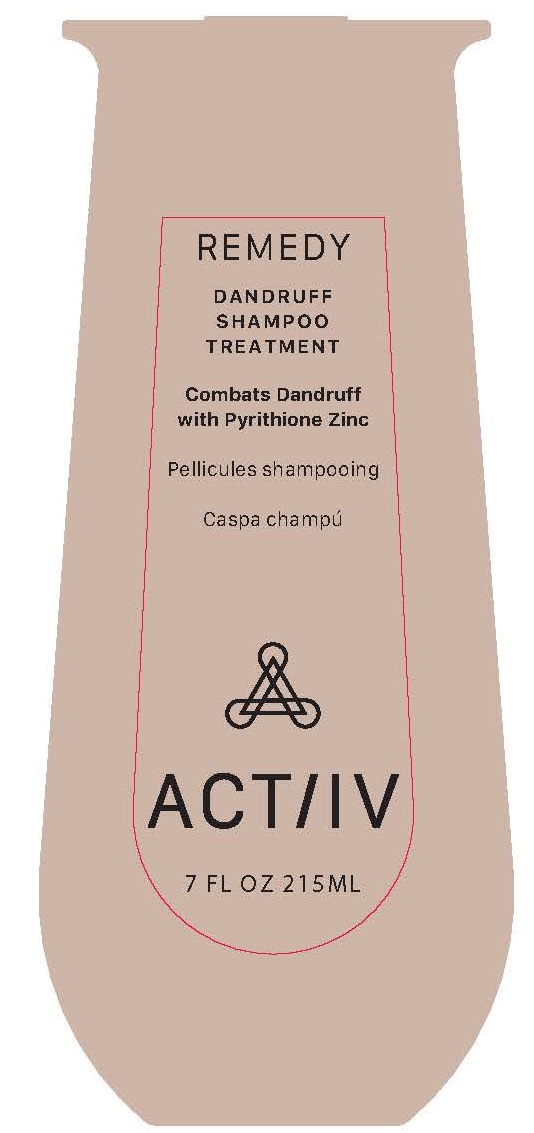 DRUG LABEL: RemedyDandruffShampooTreatment
NDC: 72496-1038 | Form: SHAMPOO
Manufacturer: Naturich Cosmetique Labs
Category: otc | Type: HUMAN OTC DRUG LABEL
Date: 20251008

ACTIVE INGREDIENTS: PYRITHIONE ZINC 10 mg/100 mL
INACTIVE INGREDIENTS: WATER 30 mL/100 mL

ACTIIV Remedy Dandruff Shampoo Treatment

Active Ingredient

Pyrithione Zinc 1.00% ..............................................................................Anti-Dandruff

Purpose:

Anti-Dandruff

When Using this product

• Avoid contact with eyes. If contact occurs, rinse eyes thoroughly with water.

Warnings

• For external use only.

Stop Use

Stop use and ask doctor if condition worsens or does not improve after regular use of this product as directed.

Keep out of reach of children. If swallowed, get medical help or contact a Poison Control Center right away.

USES

• Helps prevent recurrence of flaking and itching associated with dandruff.

Directions

• Use daily, or as directed by a doctor for maximum dandruff control.
• Massage onto wet scalp and hair, using scalp massager, if preferred. Wait 3 minutes before rinsing for best results.

Inactive Ingredients:

Water (Aqua), Sodium C14-16 Olefin Sulfonate, Decyl Glucoside, Cocamidopropyl Betaine, Propanediol, Dimethicone, Lauryl Glucoside, Glyceryl Stearate, Coco-Betaine, Jojoba Esters, Glycerin, Camellia Sinensis Leaf Extract, Serenoa Serrulata Fruit Extract, Trifolium Pratense Flower Extract, Hydrolyzed Quinoa, Mentha Arvensis Leaf Oil, Mentha Piperita (Peppermint) Oil, Glycol Distearate, Capryloyl Glycine, Laureth-4, Niacinamide, Xylitol, Xylitylglucoside, Anhydroxylitol, Menthol, Coco Nucifera (Coconut) Shell Powder, Polyacrylate Crosspolymer-6, Hexylene Glycol, Xanthan Gum, PEG-40 Castor Oil, Fragrance, Phenoxyethanol, Benzyl Alcohol, CI 42090 Acid Blue 9.

Questions?

Questions? 877-690-6466